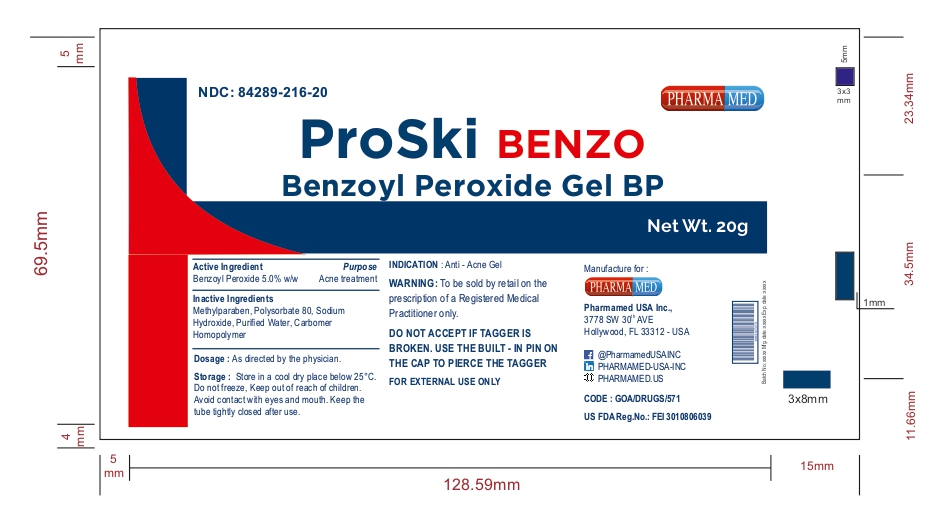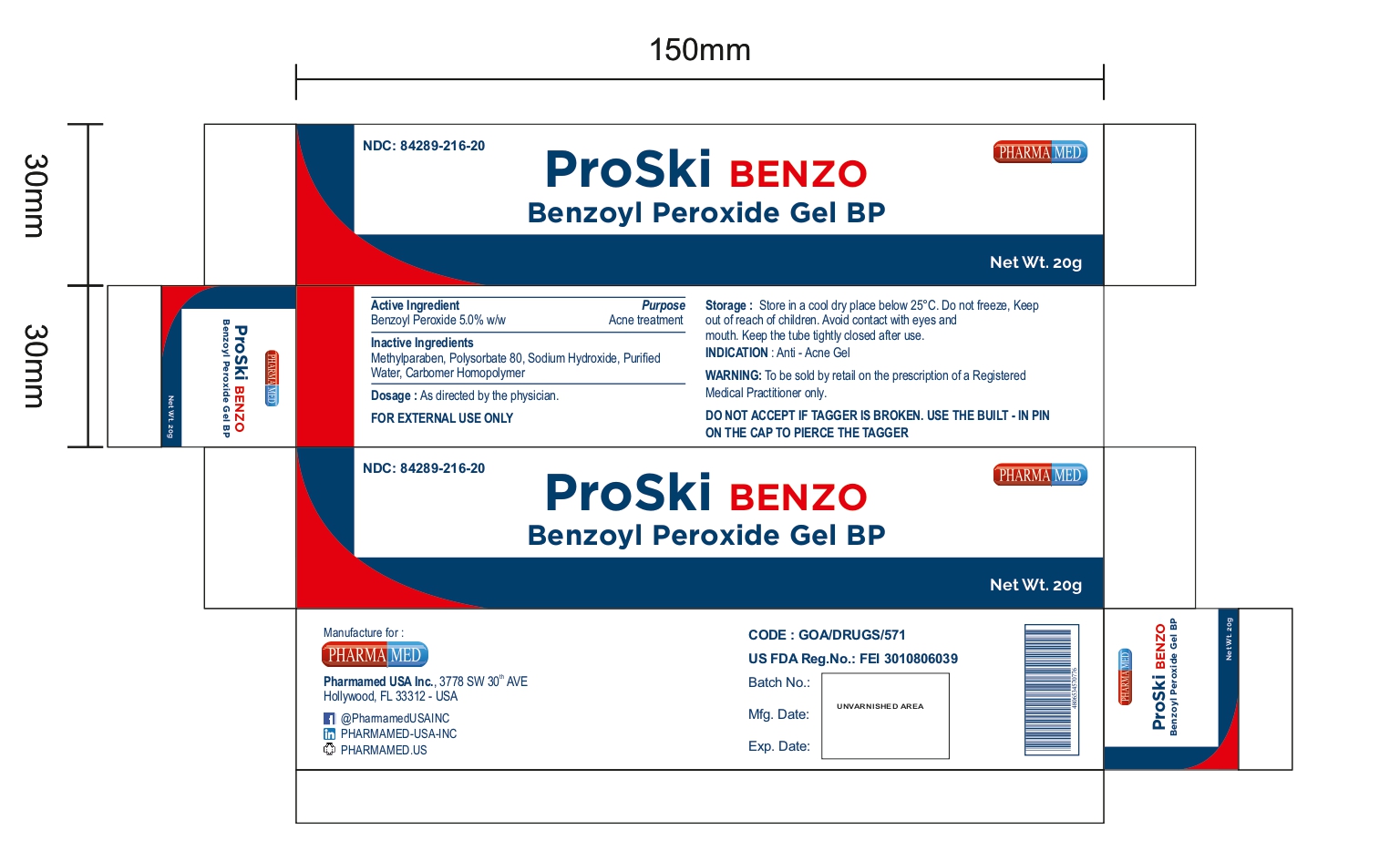 DRUG LABEL: PROSKI BENZO
NDC: 84289-216 | Form: GEL
Manufacturer: PHARMAMED USA INC
Category: otc | Type: HUMAN OTC DRUG LABEL
Date: 20250318

ACTIVE INGREDIENTS: BENZOYL PEROXIDE 5 g/100 g
INACTIVE INGREDIENTS: METHYLPARABEN; CARBOMER HOMOPOLYMER TYPE B (ALLYL SUCROSE CROSSLINKED); ROSE OIL; POLYSORBATE 80; WATER; SODIUM HYDROXIDE

BENZOYL PEROXIDE GEL BP

ACTIVE INGREDIENT

Benzoyl peroxide 5%

PURPOSE

Acne treatment

USE

For the treatment of acne

WARNING

To be sold by retail on the prescription of a Registered Medical Practitioner only

DO NOT ACCEPT IF TAGGER IS BROKEN. USE THE BUILT-IN PIN ON THE CAP TO PIERCE THE TAGGER

FOR EXTERNAL USE ONLY

Do not use

if you

- have very sensitive skin
- are sensitive to benzoyl peroxide

When using this product

- skin irritation and dryness is more likely to occur if you use another topical acne medication at the same time. If irritation occurs, only use one topical acne medication at a time.
- avoid unnecessary sun exposure and use a sunscreen
- avoid contact with the eyes, lips, and mouth
- avoid contact with hair and dyed fabrics, which may be bleached by this product
- skin irritation may occur, characterized by redness, burning, itching, peeling, or possibly swelling. Irritation may be reduced by using the product less frequently or in a lower concentration.

Stop use and ask a doctor if

- irritation becomes severe

Keep out of reach of children

Avoid contact with eyes and mouth.

Keep the tube tightly closed after use.

If swallowed, get medical help or contact a Poison Control Center right away. (1-800-222-1222)

DIRECTIONS

Sensitivity Test for a New User. Apply product sparingly to one or two small affected areas during the first 3 days. If no discomfort occurs, follow the directions stated below.
clean the skin thoroughly before applying this product
cover the entire affected area with a thin layer one to three times daily
because excessive drying of the skin may occur, start with one application daily, then gradually increase to two or three times daily if needed or as directed by a doctor
if bothersome dryness or peeling occurs, reduce application to once a day or every other day
if going outside, apply sunscreen after using this product. If irritation or sensitivity develops, stop use of both products and ask a doctor.

OTHER INFORMATION

Storage: store in a cool dry place at 20º-25ºC (68º-77ºF). Do not freeze

INACTIVE INGREDIENTS

methylparaben, polysorbate 80, sodium hydroxide, purified water, carbomer homopolymer

QUESTIONS OR COMMENTS?

(754) 200-8994 (Mon-Fri 8 AM to 4 PM EST)

PACKAGE/LABEL PRINCIPAL DISPLAY PANEL

NDC 84289-216-20

Benzoyl Peroxide Gel BP

Net Wt. 20g

GOA/DRUGS/571